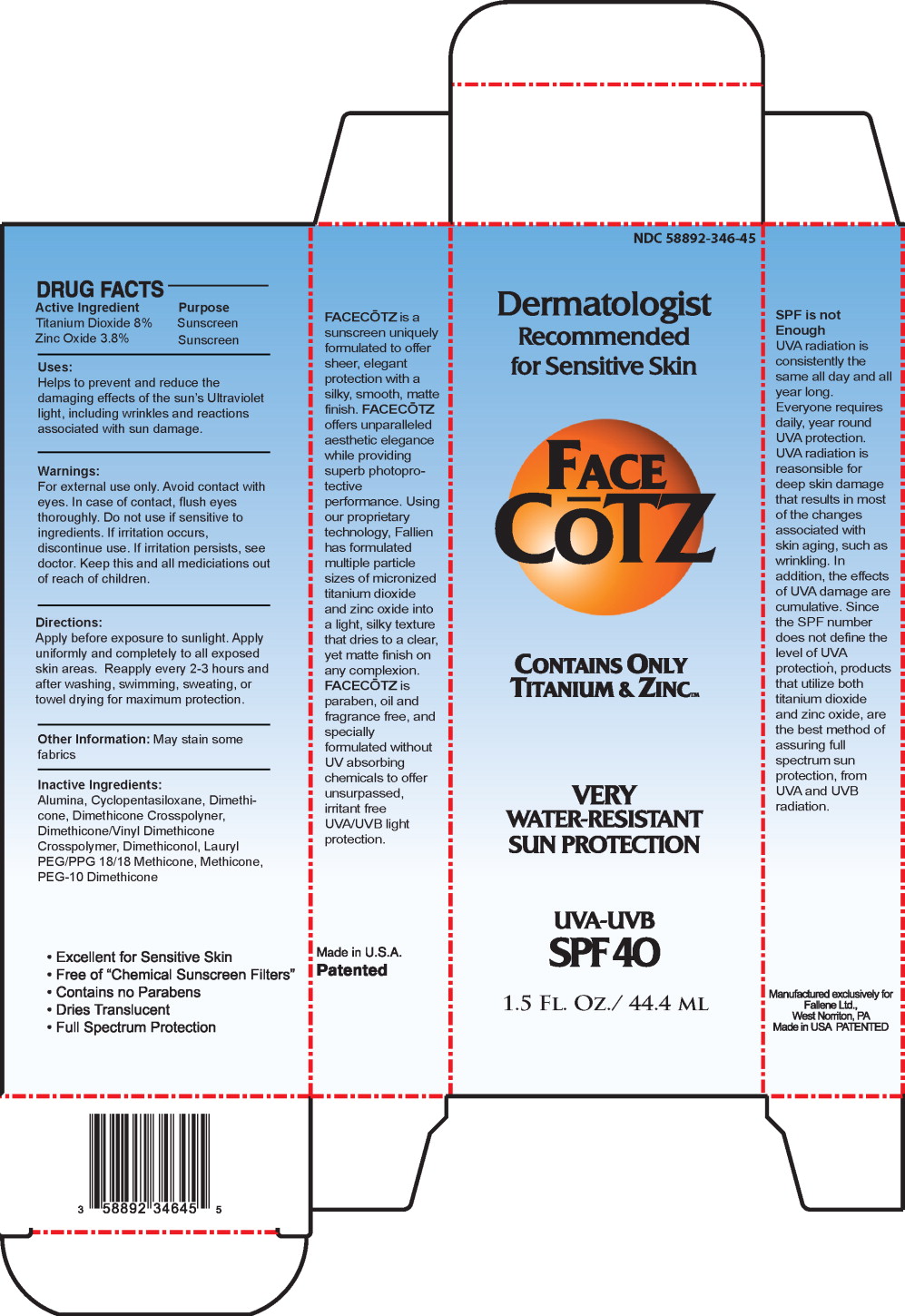 DRUG LABEL: FaceCoTZ 
NDC: 58892-346 | Form: CREAM
Manufacturer: Fallien Cosmeceuticals, LTD.
Category: otc | Type: HUMAN OTC DRUG LABEL
Date: 20100902

ACTIVE INGREDIENTS: Titanium Dioxide 85.4 mg/1 mL; Zinc Oxide 40.7 mg/1 mL
INACTIVE INGREDIENTS: Aluminum Oxide; Cyclomethicone 5; Dimethicone

FaceCŌTZ (Sunscreen)

DRUG FACTS

Active Ingredient

Titanium Dioxide 8%

Zinc Oxide 3.8%

Purpose

Sunscreen

Sunscreen

Uses:

Helps to prevent and reduce the damaging effects of the sun's Ultraviolet light, including wrinkles and reactions associated with sun damage.

Warnings:

For external use only. Avoid contact with eyes. In case of contact, flush eyes thoroughly. Do not use if sensitive to ingredients. If irritation occurs, discontinue use. If irritation persists, see doctor. Keep this and all mediciations out of reach of children.

Directions:

Apply before exposure to sunlight. Apply uniformly and completely to all exposed skin areas. Reapply every 2-3 hours and after washing, swimming, sweating, or towel drying for maximum protection.

Other Information: May stain some fabrics

Inactive Ingredients:

Alumina, Cyclopentasiloxane, Dimethicone, Dimethicone Crosspolyner, Dimethicone/Vinyl Dimethicone Crosspolymer, Dimethiconol, Lauryl PEG/PPG 18/18 Methicone, Methicone, PEG-10 Dimethicone

FACECŌTZ is a sunscreen uniquely formulated to offer sheer, elegant protection with a silky, smooth, matte finish. FACECŌTZ offers unparalleled aesthetic elegance while providing superb photoprotective performance. Using our proprietary technology, Fallien has formulated multiple particle sizes of micronized titanium dioxide and zinc oxide into a light, silky texture that dries to a clear, yet matte finish on any complexion. FACECŌTZ is paraben, oil and fragrance free, and specially formulated without UV absorbing chemicals to offer unsurpassed, irritant free UVA/UVB light protection.

SPF is not Enough

UVA radiation is consistently the same all day and all year long. Everyone requires daily, year round UVA protection. UVA radiation is reasonsible for deep skin damage that results in most of the changes associated with skin aging, such as wrinkling. In addition, the effects of UVA damage are cumulative. Since the SPF number does not define the level of UVA protection, products that utilize both titanium dioxide and zinc oxide, are the best method of assuring full spectrum sun protection, from UVA and UVB radiation.

- Excellent for Sensitive Skin
- Free of "Chemical Sunscreen Filters"
- Contains no Parabens
- Dries Translucent
- Full Spectrum Protection

Made in U.S.A.

Patented

Manufactured exclusively for
Fallene Ltd.,
West Norriton, PA
Made in USA PATENTED

Principal Display Panel – Carton Label

NDC 58892-346-45

Dermatologist

Recommended for Sensitive Skin

FACE

CŌTZ

Contains Only Titanium & ZincTM

VERY WATER-RESISTANT SUN PROTECTION

UVA-UVB

SPF40

1.5 FL. OZ./44.4 ML